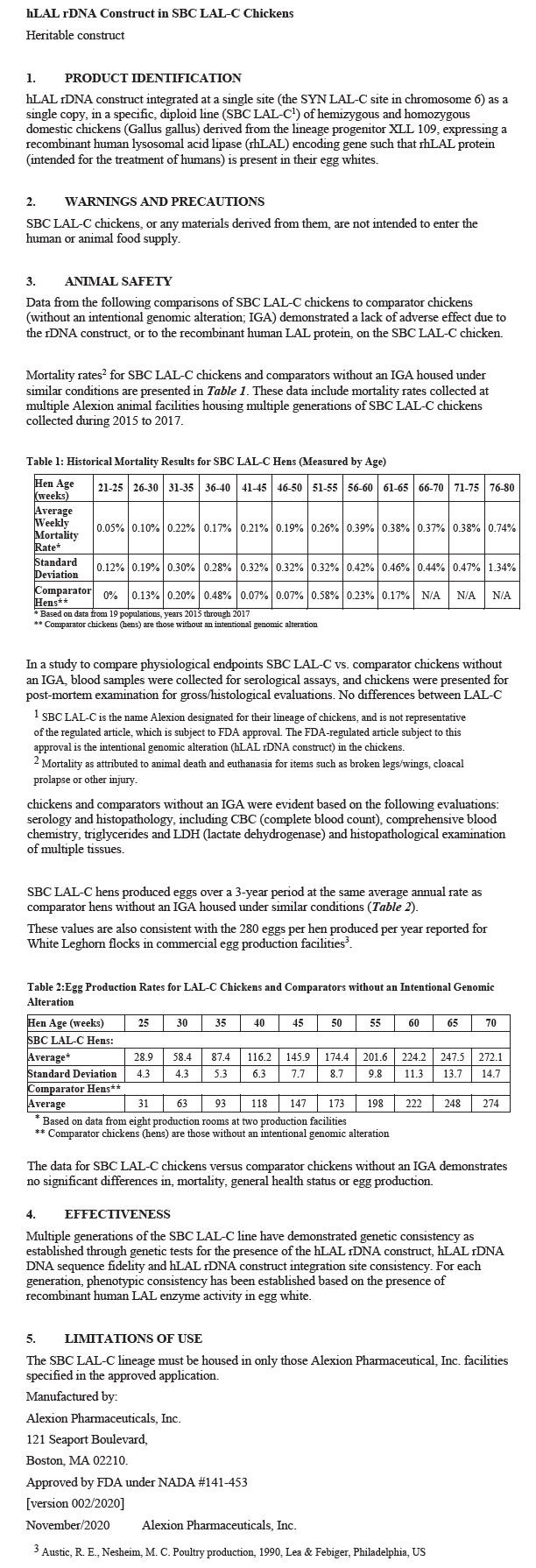 DRUG LABEL: hLAL rDNA Construct in SBC LAL-C Chickens
NDC: 25682-020 | Form: NOT APPLICABLE
Manufacturer: Alexion Pharmaceuticals, Inc.
Category: other | Type: INTENTIONAL ANIMAL GENOMIC ALTERATION LABEL
Date: 20241022

ACTIVE INGREDIENTS: HLAL RDNA CONSTRUCT IN SBC LAL-C CHICKEN 1 [arb'U]/1 [arb'U]

hLAL rDNA Construct in SBC LAL-C Chickens

Heritable construct

1. PRODUCT IDENTIFICATION

hLAL rDNA construct integrated at a single site (the SYN LAL-C site in chromosome 6) as a single copy, in a specific, diploid line (SBC LAL-C [SBC LAL-C is the name Alexion designated for their lineage of chickens, and is not representative of the regulated article, which is subject to FDA approval. The FDA-regulated article subject to this approval is the intentional genomic alteration (hLAL rDNA construct) in the chickens.]) of hemizygous and homozygous domestic chickens (Gallus gallus) derived from the lineage progenitor XLL 109, expressing a recombinant human lysosomal acid lipase (rhLAL) encoding gene such that rhLAL protein (intended for the treatment of humans) is present in their egg whites.

2. WARNINGS AND PRECAUTIONS

SBC LAL-C chickens, or any materials derived from them, are not intended to enter the human or animal food supply.

3. ANIMAL SAFETY

Data from the following comparisons of SBC LAL-C chickens to comparator chickens (without an intentional genomic alteration; IGA) demonstrated a lack of adverse effect due to the rDNA construct, or to the recombinant human LAL protein, on the SBC LAL-C chicken.

Mortality rates [Mortality as attributed to animal death and euthanasia for items such as broken legs/wings, cloacal prolapse or other injury.] for SBC LAL-C chickens and comparators without an IGA housed under similar conditions are presented in Table 1. These data include mortality rates collected at multiple Alexion animal facilities housing multiple generations of SBC LAL-C chickens collected during 2015 to 2017.

Table 1: Historical Mortality Results for SBC LAL-C Hens (Measured by Age)
Hen Age (weeks) | 21-25 | 26-30 | 31-35 | 36-40 | 41-45 | 46-50 | 51-55 | 56-60 | 61-65 | 66-70 | 71-75 | 76-80
Average Weekly Mortality Rate [Based on data from 19 populations, years 2015 through 2017] | 0.05% | 0.10% | 0.22% | 0.17% | 0.21% | 0.19% | 0.26% | 0.39% | 0.38% | 0.37% | 0.38% | 0.74%
Standard Deviation | 0.12% | 0.19% | 0.30% | 0.28% | 0.32% | 0.32% | 0.32% | 0.42% | 0.46% | 0.44% | 0.47% | 1.34%
Comparator Hens [Comparator chickens (hens) are those without an intentional genomic alteration] | 0% | 0.13% | 0.20% | 0.48% | 0.07% | 0.07% | 0.58% | 0.23% | 0.17% | N/A | N/A | N/A

In a study to compare physiological endpoints SBC LAL-C vs. comparator chickens without an IGA, blood samples were collected for serological assays, and chickens were presented for post-mortem examination for gross/histological evaluations. No differences between LAL-C chickens and comparators without an IGA were evident based on the following evaluations: serology and histopathology, including CBC (complete blood count), comprehensive blood chemistry, triglycerides and LDH (lactate dehydrogenase) and histopathological examination of multiple tissues.

SBC LAL-C hens produced eggs over a 3-year period at the same average annual rate as comparator hens without an IGA housed under similar conditions (Table 2).

These values are also consistent with the 280 eggs per hen produced per year reported for White Leghorn flocks in commercial egg production facilities [Austic, R. E., Nesheim, M. C. Poultry production, 1990, Lea & Febiger, Philadelphia, US] .

Table 2:Egg Production Rates for LAL-C Chickens and Comparators without an Intentional Genomic Alteration
Hen Age (weeks) | 25 | 30 | 35 | 40 | 45 | 50 | 55 | 60 | 65 | 70
SBC LAL-C Hens:
Average [Based on data from eight production rooms at two production facilities] | 28.9 | 58.4 | 87.4 | 116.2 | 145.9 | 174.4 | 201.6 | 224.2 | 247.5 | 272.1
Standard Deviation | 4.3 | 4.3 | 5.3 | 6.3 | 7.7 | 8.7 | 9.8 | 11.3 | 13.7 | 14.7
Comparator Hens [Comparator chickens (hens) are those without an intentional genomic alteration]
Average | 31 | 63 | 93 | 118 | 147 | 173 | 198 | 222 | 248 | 274

The data for SBC LAL-C chickens versus comparator chickens without an IGA demonstrates no significant differences in, mortality, general health status or egg production.

4. EFFECTIVENESS

Multiple generations of the SBC LAL-C line have demonstrated genetic consistency as established through genetic tests for the presence of the hLAL rDNA construct, hLAL rDNA DNA sequence fidelity and hLAL rDNA construct integration site consistency. For each generation, phenotypic consistency has been established based on the presence of recombinant human LAL enzyme activity in egg white.

5. LIMITATIONS OF USE

The SBC LAL-C lineage must be housed in only those Alexion Pharmaceutical, Inc. facilities specified in the approved application.

Manufactured by:

Alexion Pharmaceuticals, Inc.

121 Seaport Boulevard,

Boston, MA 02210.

Approved by FDA under NADA #141-453

[version 002/2020]

November/2020
Alexion Pharmaceuticals, Inc.